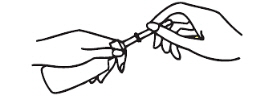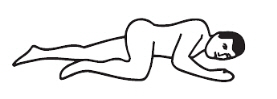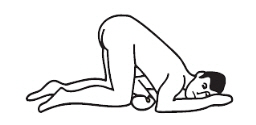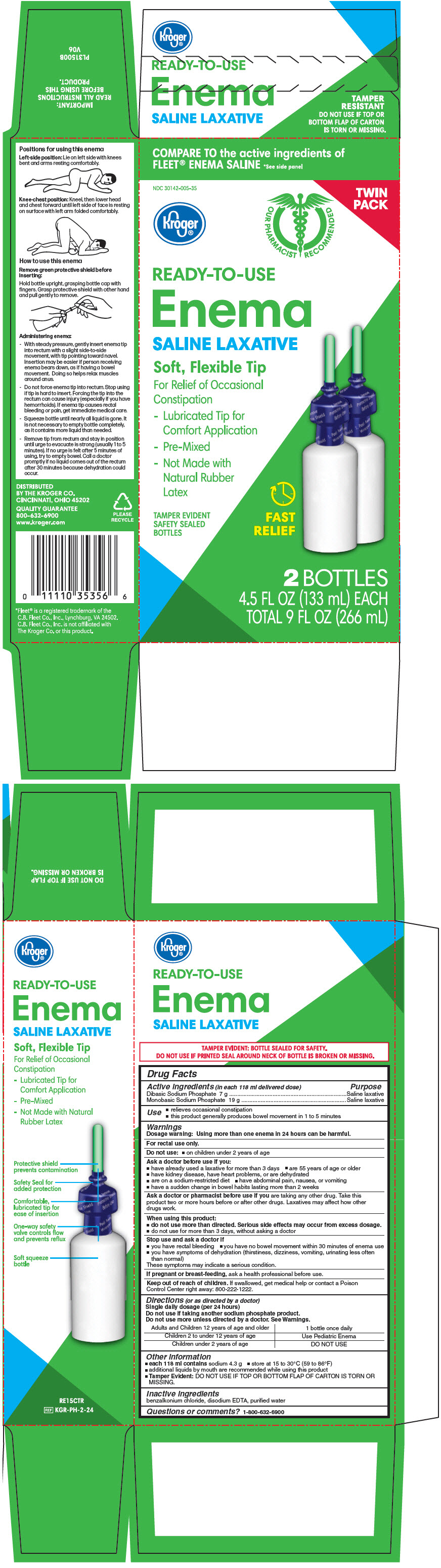 DRUG LABEL: Saline Laxative
NDC: 30142-005 | Form: ENEMA
Manufacturer: Kroger Company
Category: otc | Type: HUMAN OTC DRUG LABEL
Date: 20200123

ACTIVE INGREDIENTS: SODIUM PHOSPHATE, DIBASIC, UNSPECIFIED FORM 7 g/118 mL; SODIUM PHOSPHATE, MONOBASIC, UNSPECIFIED FORM 19 g/118 mL
INACTIVE INGREDIENTS: BENZALKONIUM CHLORIDE; EDETATE DISODIUM; WATER

Drug Facts

Active ingredient

(in each 118 mL delivered dose)

Dibasic sodium phosphate 7 g

Monobasic sodium phosphate 19 g

Purpose

Saline laxative

Uses

- relieves occasional constipation

Warnings

For rectal use only

Ask a doctor before use if you have

- a sodium-restricted diet
- abdominal pain, nausea or vomiting
- kidney disease, heart problems, or are dehydrated
- noticed a sudden change in bowel habits that lasts over 2 weeks

Ask a doctor or pharmacist before use if you are

taking any other drug. Take this product two or more hours before or after other drugs. Laxatives may affect how other drugs work.

When using this product

- do not use more than directed. Serious side effects may occur from excess dosage.
- do not use for more than 3 days

Stop use and ask a doctor if

- you have rectal bleeding
- you have no bowel movement after use of a laxative

These may be signs of a serious condition.

Keep out of reach of children.

If swallowed, get medical help or contact a Poison Control Center right away. (1-800-222-1222)

Directions

Do not use more unless directed by a doctor. See Warnings.

adults & children; 12 years and over | one bottle once daily
children 2 to under; 12 years | 1/2 bottle once daily; Discard unused portion
children under; 2 years | do not use

CAUTION:

Remove green protective shield before inserting. Hold bottle upright, grasping bottle cap with fingers. Grasp protective shield with other hand and pull gently to remove.

Positioning:

Left-side position: lie on left side with knee bent and arms at rest.

Knee-chest position: kneel, then lower head and chest forward until left side of face is resting on surface. Position arms comfortably.

Administering enema:

- with steady pressure, gently insert enema with tip pointing toward navel.
- squeeze bottle until recommended dose is expelled (it is not necessary to empty unit completely. Bottle contains more liquid than needed for effective use. A small amount of liquid will remain in bottle after squeezing).
- remove tip from rectum
- stop using if tip is hard to insert. Forcing the tip into the rectum can cause injury (especially if you have hemorrhoids). If enema tip causes rectal bleeding or pain, get immediate medical care.
- maintain position until urge to evacuate is strong (usually 1 to 5 minutes)
- if no urge is felt after 5 minutes of using, try to empty bowel. Call a doctor promptly if no liquid comes out of the rectum after 30 minutes because dehydration could occur.

Other Information

- each 118 mL contains: sodium 4.3 g
- store at room temperature 20-25 deg C (68-77 deg F)
- this product generally produces bowel movement in 1 to 5 minutes

Inactive ingredients

benzalkonium chloride, disodium EDTA, purified water

Questions or comments?

1-800-633-5463

PRINCIPAL DISPLAY PANEL - 2 Bottle Carton

COMPARE TO the active ingredients of
FLEET® ENEMA SALINE *See side panel

NDC 30142-005-35

TWIN
PACK

Kroger®

OUR PHARMACIST RECOMMENDED

READY-TO-USE
Enema
SALINE LAXATIVE

Soft, Flexible Tip

For Relief of Occasional
Constipation

- Lubricated Tip for
  Comfort Application
- Pre-Mixed
- Not Made with
  Natural Rubber
  Latex

TAMPER EVIDENT
SAFETY SEALED
BOTTLES

FAST
RELIEF

2 BOTTLES
4.5 FL OZ (133 ml) EACH
TOTAL 9 FL OZ (266 mL)